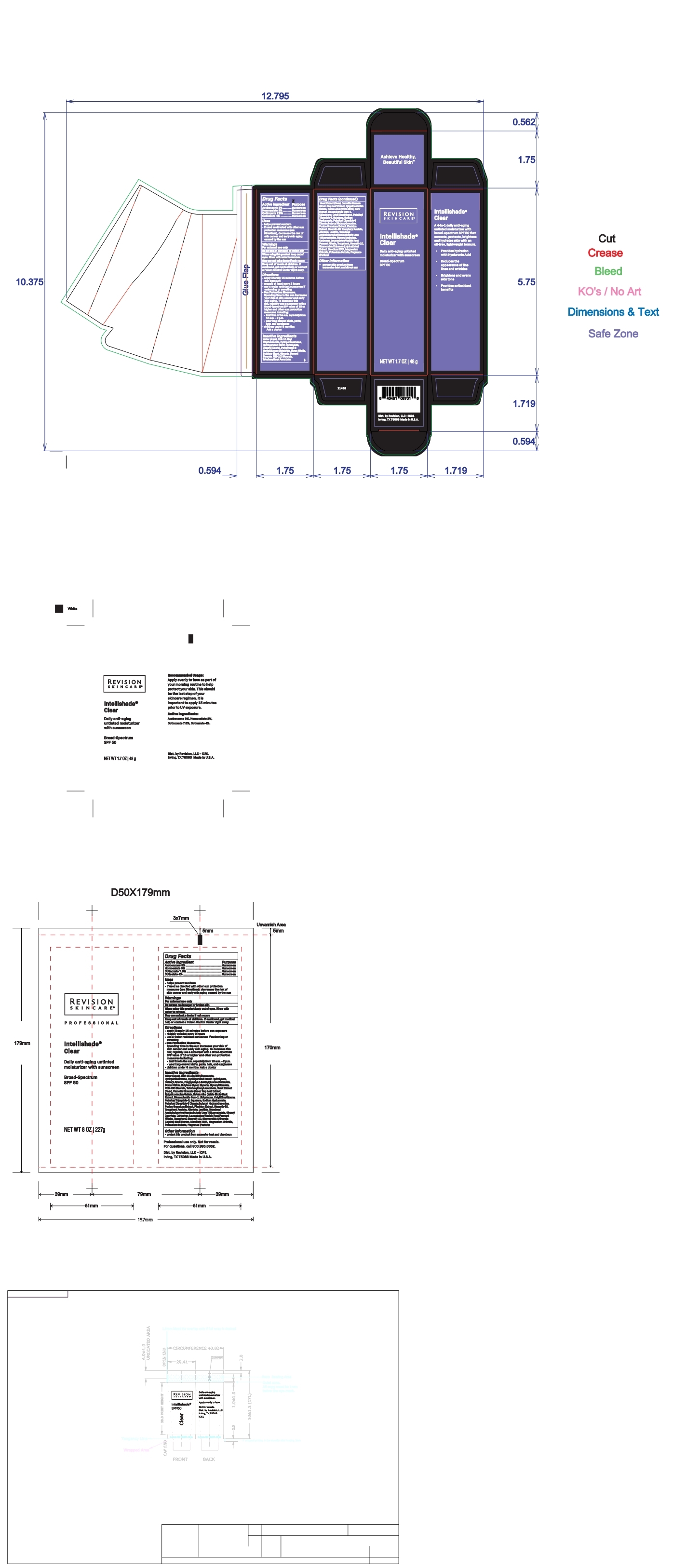 DRUG LABEL: Intellishade Clear SPF 50
NDC: 64651-7720 | Form: CREAM
Manufacturer: Revision, LLC
Category: otc | Type: HUMAN OTC DRUG LABEL
Date: 20260113

ACTIVE INGREDIENTS: OCTINOXATE 7.5 g/100 g; OCTISALATE 4 g/100 g; AVOBENZONE 3 g/100 g; HOMOSALATE 3 g/100 g
INACTIVE INGREDIENTS: CYCLOMETHICONE 5; CETOSTEARYL ALCOHOL; BORON NITRIDE; WATER; SORBITOL; GLYCERIN; GLYCERYL MONOSTEARATE; PEG-100 STEARATE; BUTYLENE GLYCOL; TETRAHEXYLDECYL ASCORBATE; YEAST; GREEN TEA LEAF; EPIGALLOCATECHIN GALLATE; BETULA PUBESCENS BARK; BIOSACCHARIDE GUM-1; UBIDECARENONE; CETYL DIMETHICONE 25; PALMITOYL TRIPEPTIDE-5; SQUALANE; HYALURONATE SODIUM; PALMITOYLLYSYLVALYLDIAMINOBUTYROYLTHREONINE; POMEGRANATE; STEARETH-20; .ALPHA.-TOCOPHEROL ACETATE; ALLANTOIN; LECITHIN, SOYBEAN; GLYCERYL CAPRYLATE; CARBOMER INTERPOLYMER TYPE A (ALLYL SUCROSE CROSSLINKED); TOCOPHEROL; STEARETH-10; SIMMONDSIA CHINENSIS SEED; EDETATE DISODIUM; MAGNESIUM CHLORIDE; POTASSIUM SORBATE

Intellishade Clear SPF 50

Revision Siincare Intellishade Clear Spectrum SPF 50 1.7 oz

ITC_carton_retail_ICC2_V5_OL

ITC_retail_tube_ICR4_V1_OL

Anti-aging untinted

daily moisturizer

with sunscreen

Broad-Spectrum
SPF 50

Moisturize + Protect

NET WT 1.7 OZ | 48 g

Active ingredient Purpose

Avobenzone 3% ........... Sunscreen
Homosalate 3% ............ Sunscreen
Octinoxate 7.5% .......... Sunscreen
Octisalate 4% ............... Sunscreen

Uses

• helps prevent sunburn
• if used as directed with other sun protection measures (see Directions), decreases the risk of skin cancer and early skin aging caused by the sun

Warnings

For external use only

Do not useon damaged or broken skin

WHEN USING

When using this productkeep out of eyes. Rinse with water to remove.

Stop use and ask a doctorif rash occurs

Keep out of reach of children.If swallowed, get medical help or contact a Poison Control Center right away.

Directions
• apply liberally 15 minutes before sun exposure
• reapply at least every 2 hours
• use a water resistant sunscreen if swimming or sweating
• Sun Protection Measures.
Spending time in the sun increases your risk of skin cancer and early skin aging. To decrease this risk, regularly use a sunscreen
with a Broad-Spectrum SPF value of 15 or higher and other sun protection measures including:
• limit time in the sun, especially from 10 a.m. – 2 p.m.
• wear long-sleeved shirts, pants, hats, and sunglasses
• children under 6 months: Ask a doctor

INACTIVE INGREDIENT

Water (Aqua), C12-15 Alkyl Ethylhexanoate, Cyclopentasiloxane, Hydrogenated Starch Hydrolysate, Cetearyl Alcohol, Polyglyceryl-3 Methylglucose Distearate, Boron Nitride, Glycerin, Butylene Glycol, Glyceryl Stearate, PEG-100 Stearate, Tetrahexyldecyl Ascorbate, Yeast Extract (Faex), Camellia Sinensis Leaf Extract, Epigallocatechin Gallate, Betula Alba Bark Extract, Biosaccharide Gum-1, Ubiquinone, Cetyl Dimethicone, Palmitoyl Tripeptide-5, Squalane, Sodium Hyaluronate, Palmitoyl Dipeptide-5 Diaminobutyroyl Hydroxythreonine, Punica Granatum Fruit Extract, Plankton Extract, Steareth-20, Tocopheryl Acetate, Allantoin, Lecithin, Tetradecyl Aminobutyroylvalylaminobutyric Urea Acetate, Glyceryl Caprylate, Carbomer, Leuconostoc/Radish Root Ferment Filtrate, Tocopherol, Steareth-10, Simmondsia Chinensis (Jojoba) Meal Extract, Disodium EDTA, Magnesium Chloride, Potassium Sorbate, Fragrance (Parfum), Benzyl Benzoate, Citronellol, Hexamethylindanopyran, Hexyl Cinnamal, Limonene, Linalool, Linalyl Acetate, Tetramethyl Acetyloctahydronaphthalenes

Other information
• protect this product from excessive heat and direct sun

Dist. by Revision, LP
Irving, TX 75063 Made in U.S.A.

Revision Siincare Intellishade Clear Spectrum SPF 50 8 oz

ITC_pro_tube_ICP4

Anti-aging untinted

daily moisturizer

with sunscreen

Broad-Spectrum
SPF 50

Moisturize + Protect

NET WT 1.7 OZ | 48 g

Active ingredient Purpose

Avobenzone 3% ........... Sunscreen
Homosalate 3% ............ Sunscreen
Octinoxate 7.5% .......... Sunscreen
Octisalate 4% ............... Sunscreen

Uses

• helps prevent sunburn
• if used as directed with other sun protection measures (see Directions), decreases the risk of skin cancer and early skin aging caused by the sun

Warnings

For external use only

Do not useon damaged or broken skin

WHEN USING

When using this productkeep out of eyes. Rinse with water to remove.

Stop use and ask a doctorif rash occurs

Keep out of reach of children.If swallowed, get medical help or contact a Poison Control Center right away.

Directions
• apply liberally 15 minutes before sun exposure
• reapply at least every 2 hours
• use a water resistant sunscreen if swimming or sweating
• Sun Protection Measures.
Spending time in the sun increases your risk of skin cancer and early skin aging. To decrease this risk, regularly use a sunscreen
with a Broad-Spectrum SPF value of 15 or higher and other sun protection measures including:
• limit time in the sun, especially from 10 a.m. – 2 p.m.
• wear long-sleeved shirts, pants, hats, and sunglasses
• children under 6 months: Ask a doctor

INACTIVE INGREDIENT

Water (Aqua), C12-15 Alkyl Ethylhexanoate, Cyclopentasiloxane, Hydrogenated Starch Hydrolysate, Cetearyl Alcohol, Polyglyceryl-3 Methylglucose Distearate, Boron Nitride, Glycerin, Butylene Glycol, Glyceryl Stearate, PEG-100 Stearate, Tetrahexyldecyl Ascorbate, Yeast Extract (Faex), Camellia Sinensis Leaf Extract, Epigallocatechin Gallate, Betula Alba Bark Extract, Biosaccharide Gum-1, Ubiquinone, Cetyl Dimethicone, Palmitoyl Tripeptide-5, Squalane, Sodium Hyaluronate, Palmitoyl Dipeptide-5 Diaminobutyroyl Hydroxythreonine, Punica Granatum Fruit Extract, Plankton Extract, Steareth-20, Tocopheryl Acetate, Allantoin, Lecithin, Tetradecyl Aminobutyroylvalylaminobutyric Urea Acetate, Glyceryl Caprylate, Carbomer, Leuconostoc/Radish Root Ferment Filtrate, Tocopherol, Steareth-10, Simmondsia Chinensis (Jojoba) Meal Extract, Disodium EDTA, Magnesium Chloride, Potassium Sorbate, Fragrance (Parfum), Benzyl Benzoate, Citronellol, Hexamethylindanopyran, Hexyl Cinnamal, Limonene, Linalool, Linalyl Acetate, Tetramethyl Acetyloctahydronaphthalenes

Other information
• protect this product from excessive heat and direct sun

Dist. by Revision, LP
Irving, TX 75063 Made in U.S.A.

DOSAGE AND ADMINISTRATION

apply liberally 15 minutes before sun exposure
reapply at least every two hours
use a water resistant sunscreen if swimming or sweating

PURPOSE

Anti-aging untinted daily moisturizer with sunscreen

Broad Spectrum

SPF 50